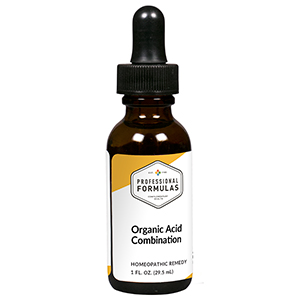 DRUG LABEL: Organic Acid Combination
NDC: 63083-9305 | Form: LIQUID
Manufacturer: Professional Complementary Health Formulas
Category: homeopathic | Type: HUMAN OTC DRUG LABEL
Date: 20190815

ACTIVE INGREDIENTS: GELSEMIUM SEMPERVIRENS ROOT 3 [hp_X]/29.5 mL; SODIUM CARBONATE 3 [hp_X]/29.5 mL; STRYCHNOS NUX-VOMICA SEED 6 [hp_X]/29.5 mL; CHELIDONIUM MAJUS WHOLE 10 [hp_X]/29.5 mL; ADIPIC ACID 12 [hp_X]/29.5 mL; CAPRYLIC ACID 12 [hp_X]/29.5 mL; PARAFFINS, CHLORO- 12 [hp_X]/29.5 mL; SORBIC ACID 12 [hp_X]/29.5 mL; SULFUR 12 [hp_X]/29.5 mL
INACTIVE INGREDIENTS: ALCOHOL; WATER

R305

ACTIVE INGREDIENTS

Gelsemium sempervirens 3X
Natrum carbonicum 3X
Nux vomica 6X
Chelidonium majus 10X
Adipic acid 12X
Caprylic acid 12X
Paraffin 12X
Sorbicum acid 12X
Sulphur 12X

QUESTIONS

Professional Formulas

PO Box 2034 Lake Oswego, OR 97035

INDICATIONS

For the temporary relief of watery eyes, wheezing, runny nose, cough, minor sore throat, red or irritated skin or eyes, indigestion, or nausea.*

PURPOSE

*Claims based on traditional homeopathic practice, not accepted medical evidence. Not FDA evaluated.

WARNINGS

Consult a doctor if condition worsens or if symptoms persist. Keep out of the reach of children. In case of overdose, get medical help or contact a poison control center right away. If pregnant or breastfeeding, ask a healthcare professional before use.

Keep out of the reach of children.

PREGNANCY OR BREAST FEEDING

If pregnant or breastfeeding, ask a healthcare professional before use.

DIRECTIONS

Place drops under tongue 30 minutes before/after meals. Adults and children 12 years and over: Take 10 drops up to 3 times per day. Consult a physician for use in children under 12 years of age.

OTHER INFORMATION

Tamper resistant. If seal is broken, do not use. After opening, close container tightly and store at room temperature away from heat.

INACTIVE INGREDIENTS

40% ethanol, purified water.

LABEL

Est 1985

Professional Formulas

Complementary Health

Organic Acid Combination

Homeopathic Remedy

1 FL. OZ. (29.5 mL)